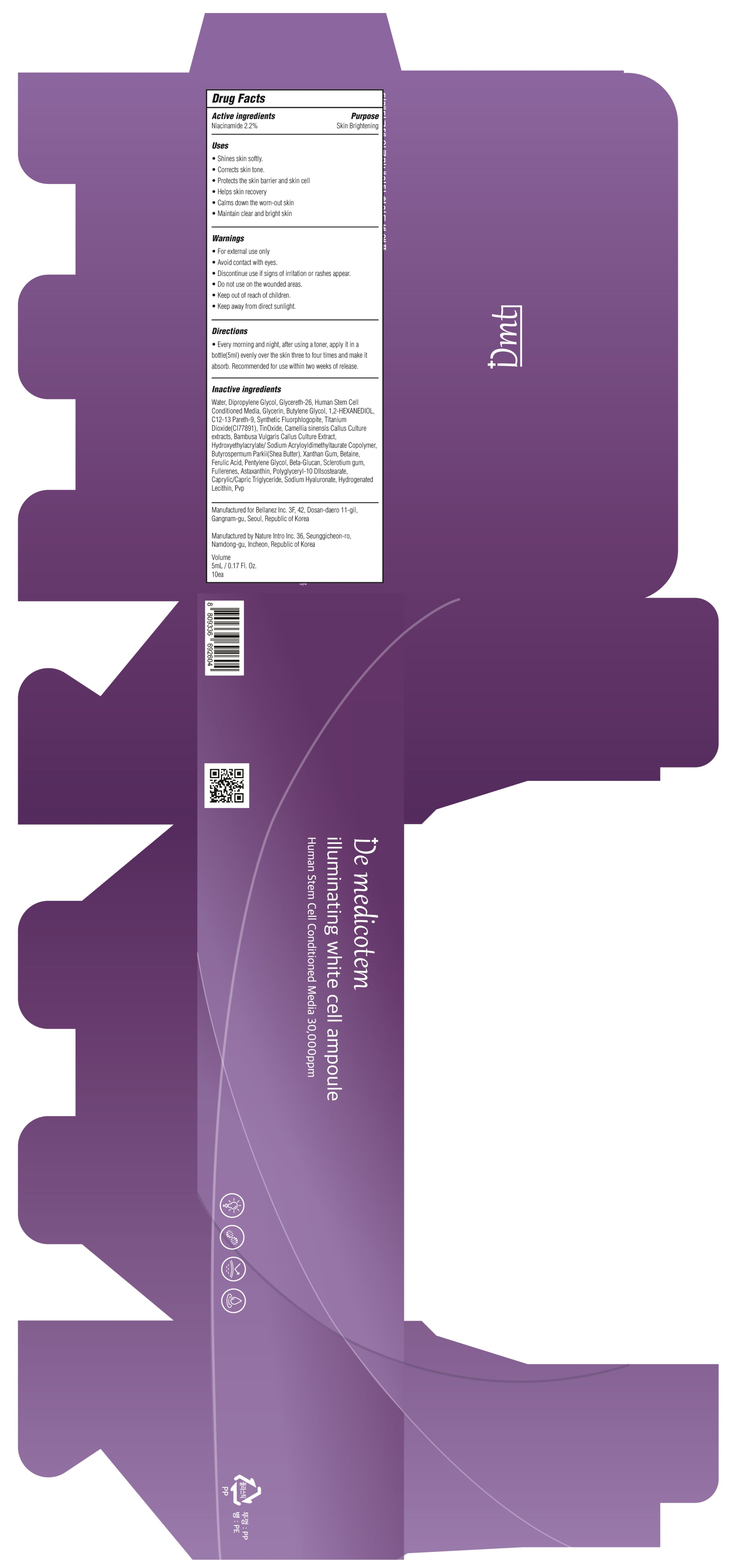 DRUG LABEL: De medicotem illuminating white cell ampoule
NDC: 72799-010 | Form: LIQUID
Manufacturer: BELLANEZ
Category: otc | Type: HUMAN OTC DRUG LABEL
Date: 20190130

ACTIVE INGREDIENTS: NIACINAMIDE 0.11 g/5 mL
INACTIVE INGREDIENTS: Water; Dipropylene Glycol

ACTIVE INGREDIENT

Active ingredients: Niacinamide 2.2%

INACTIVE INGREDIENT

Inactive ingredients:
Water, Dipropylene Glycol, Glycereth-26, Human Stem Cell Conditioned Media, Glycerin, Butylene Glycol, 1,2-HEXANEDIOL, C12-13 Pareth-9, Synthetic Fluorphlogopite, Titanium Dioxide(CI77891), TinOxide, Camellia sinensis Callus Culture extracts, Bambusa Vulgaris Callus Culture Extract, Hydroxyethylacrylate/ Sodium Acryloyldimethyltaurate Copolymer, Butyrospermum Parkii(Shea Butter), Xanthan Gum, Betaine, Ferulic Acid, Pentylene Glycol, Beta-Glucan, Sclerotium gum, Fullerenes, Astaxanthin, Polyglyceryl-10 DIIsostearate, Caprylic/Capric Triglyceride, Sodium Hyaluronate, Hydrogenated Lecithin, Pvp

PURPOSE

Purpose: Skin Brightening

WARNINGS

For external use only
Avoid contact with eyes.
Discontinue use if signs of irritation or rashes appear.
Do not use on the wounded areas.
Keep out of reach of children.
Keep away from direct sunlight

KEEP OUT OF REACH OF CHILDREN

Uses

■ Shines skin softly.
■ Corrects skin tone.
■ Protects the skin barrier and skin cell
■ Helps skin recovery
■ Calms down the worn-out skin
■ Maintain clear and bright skin

Directions

■ Every morning and night, after using a toner, apply it in a bottle(5ml) evenly over the skin three to four times and make it absorb. Recommended for use within two weeks of release.